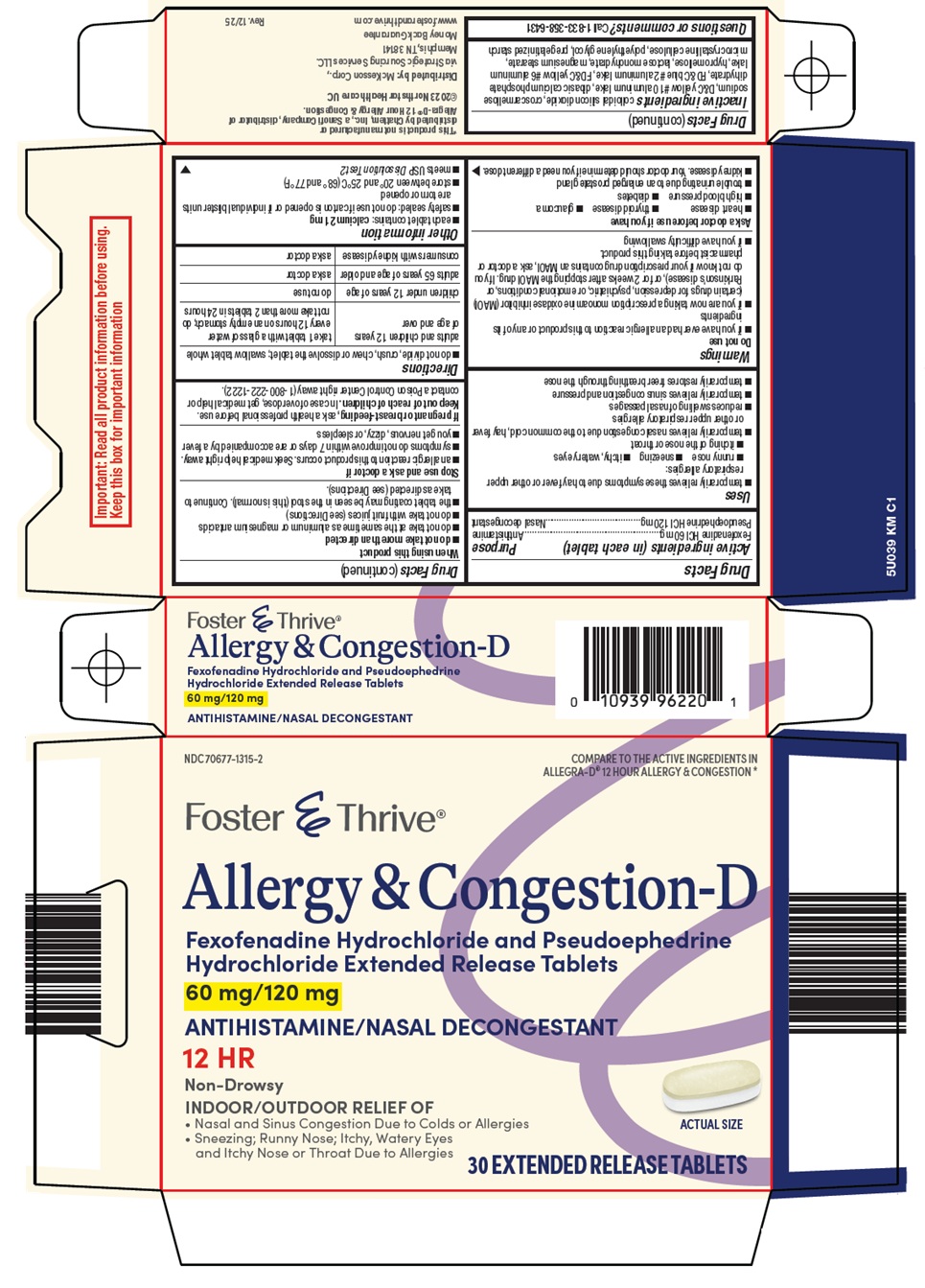 DRUG LABEL: FOSTER AND THRIVE ALLERGY AND CONGESTION D
NDC: 70677-1315 | Form: TABLET, FILM COATED, EXTENDED RELEASE
Manufacturer: Strategic Sourcing Services LLC
Category: otc | Type: HUMAN OTC DRUG LABEL
Date: 20260211

ACTIVE INGREDIENTS: FEXOFENADINE HYDROCHLORIDE 60 mg/1 1; PSEUDOEPHEDRINE HYDROCHLORIDE 120 mg/1 1
INACTIVE INGREDIENTS: SILICON DIOXIDE; CROSCARMELLOSE SODIUM; D&C YELLOW NO. 10 ALUMINUM LAKE; DIBASIC CALCIUM PHOSPHATE DIHYDRATE; FD&C BLUE NO. 2 ALUMINUM LAKE; FD&C YELLOW NO. 6 ALUMINUM LAKE; HYPROMELLOSE, UNSPECIFIED; LACTOSE MONOHYDRATE; MAGNESIUM STEARATE; MICROCRYSTALLINE CELLULOSE; POLYETHYLENE GLYCOL, UNSPECIFIED

McKesson Allergy & Congestion-D Drug Facts

Active ingredients (in each tablet)

Fexofenadine HCl 60 mg

Pseudoephedrine HCl 120 mg

Purpose

Antihistamine

Nasal decongestant

Uses

- temporarily relieves these symptoms due to hay fever or other upper respiratory allergies:
  - runny nose
  - sneezing
  - itchy, watery eyes
  - itching of the nose or throat
- temporarily relieves nasal congestion due to the common cold, hay fever or other upper respiratory allergies
- reduces swelling of nasal passages
- temporarily relieves sinus congestion and pressure
- temporarily restores freer breathing through the nose

Warnings

Do not use

- if you have ever had an allergic reaction to this product or any of its ingredients
- if you are now taking a prescription monoamine oxidase inhibitor (MAOI) (certain drugs for depression, psychiatric, or emotional conditions, or Parkinson’s disease), or for 2 weeks after stopping the MAOI drug. If you do not know if your prescription drug contains an MAOI, ask a doctor or pharmacist before taking this product.
- if you have difficulty swallowing

Ask a doctor before use if you have

- heart disease
- thyroid disease
- glaucoma
- high blood pressure
- diabetes
- trouble urinating due to an enlarged prostate gland
- kidney disease. Your doctor should determine if you need a different dose.

When using this product

- do not take more than directed
- do not take at the same time as aluminum or magnesium antacids
- do not take with fruit juices (see Directions)
- the tablet coating may be seen in the stool (this is normal). Continue to take as directed (see Directions).

Stop use and ask a doctor if

- an allergic reaction to this product occurs. Seek medical help right away.
- symptoms do not improve within 7 days or are accompanied by a fever
- you get nervous, dizzy, or sleepless

If pregnant or breast-feeding,

ask a health professional before use.

Keep out of reach of children.

In case of overdose, get medical help or contact a Poison Control Center right away (1-800-222-1222).

Directions

- do not divide, crush, chew or dissolve the tablet; swallow tablet whole

adults and children 12 years of age and over | take 1 tablet with a glass of water every 12 hours on an empty stomach; do not take more than 2 tablets in 24 hours
children under 12 years of age | do not use
adults 65 years of age and older | ask a doctor
consumers with kidney disease | ask a doctor

Other information

- each tablet contains: calcium 21 mg
- safety sealed: do not use if carton is opened or if individual blister units are torn or opened
- store between 20° and 25°C (68° and 77°F)
- meets USP Dissolution Test 2

Inactive ingredients

colloidal silicon dioxide, croscarmellose sodium, D&C yellow #10 aluminum lake, dibasic calcium phosphate dihydrate, FD&C blue #2 aluminum lake, FD&C yellow #6 aluminum lake, hypromellose, lactose monohydrate, magnesium stearate, microcrystalline cellulose, polyethylene glycol, pregelatinized starch

Questions or comments?

Call 1-833-358-6431

Package/Label Principal Display Panel

COMPARE TO THE ACTIVE INGREDIENTS IN ALLEGRA-D® 12 HOUR ALLERGY & CONGESTION

Foster & Thrive®

Allergy & Congestion-D

Fexofenadine Hydrochloride and Pseudoephedrine Hydrochloride Extended Release Tablets

60 mg/120 mg

ANTIHISTAMINE/NASAL DECONGESTANT

12 HR

Non-Drowsy

INDOOR/OUTDOOR RELIEF OF

• Nasal and Sinus Congestion Due to Colds or Allergies

• Sneezing; Runny Nose; Itchy, Watery Eyes and Itchy Nose or Throat Due to Allergies

ACTUAL SIZE

30 EXTENDED RELEASE TABLETS